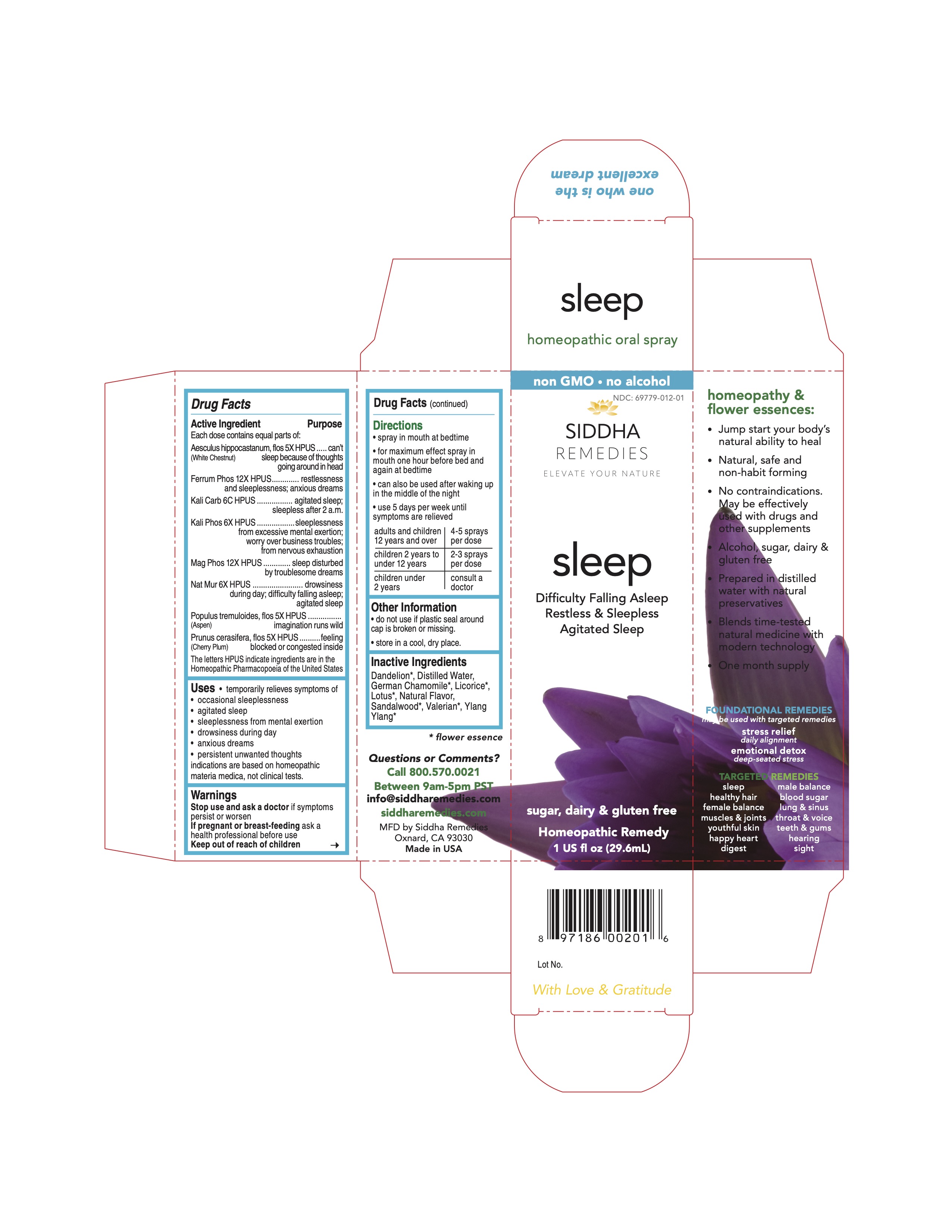 DRUG LABEL: sleep
NDC: 69779-012 | Form: SPRAY
Manufacturer: Siddha Flower Essences LLC
Category: homeopathic | Type: HUMAN OTC DRUG LABEL
Date: 20251231

ACTIVE INGREDIENTS: AESCULUS HIPPOCASTANUM FLOWER 5 [hp_X]/29.6 mL; FERROSOFERRIC PHOSPHATE 12 [hp_X]/29.6 mL; POTASSIUM CARBONATE 6 [hp_C]/29.6 mL; POTASSIUM PHOSPHATE, DIBASIC 6 [hp_X]/29.6 mL; MAGNESIUM PHOSPHATE, DIBASIC TRIHYDRATE 12 [hp_X]/29.6 mL; SODIUM CHLORIDE 6 [hp_X]/29.6 mL; POPULUS TREMULA FLOWERING TOP 5 [hp_X]/29.6 mL; PRUNUS CERASIFERA FLOWER 5 [hp_X]/29.6 mL
INACTIVE INGREDIENTS: TARAXACUM OFFICINALE FLOWERING TOP; MATRICARIA RECUTITA FLOWERING TOP; LICORICE; NELUMBO NUCIFERA FLOWER; WATER; SANDALWOOD; VALERIAN; CANANGA ODORATA FLOWER

Drug Facts

Active Ingredient

Each dose contains equal parts of:

Aesculus hippocastanum, flos (White Chestnut) 5X HPUS
Ferrum Phos 12X HPUS
Kali Carb 6C HPUS
Kali Phos 6X HPUS
Mag Phos 12X HPUS
Nat Mur 6X HPUS
Populus termula, flos (Aspen) 5X HPUS
Prunus cerasifera, flos 5X HPUS

Purpose

Each dose contains equal parts of:
Aesculus hippocastanum, flos (White Chestnut) 5X HPUS.........can't sleep because of thoughts going around in head
Ferrum Phos 12X HPUS..........................................................restlessness and sleeplessness; anxious dreams
Kali Carb 6C HPUS.................................................................agitated sleep; sleepless after 2 a.m.
Kali Phos 6X HPUS................................................................sleeplessness from excessive mental exertion; worry over business troubles; from nervous exhauston
Mag Phos 12X HPUS.............................................................sleep disturbed by troublesome dreams
Nat Mur 6X HPUS..................................................................drowsiness during day; difficulty falling asleep; agitated sleep
Populus termula, flos (Aspen) 5X HPUS...................................imagination runs wild
Prunus cerasifera, flos (Cherry Plum) 5X HPUS........................feeling blocked or congested inside
The letters HPUS indicate ingredients are in the Homeopathic Pharmacopoeia of the United States.

Uses

- temporarily relieves symptoms of
- occasional sleeplessness
- agitated sleep
- sleeplessness from mental exertion
- drowsiness during day
- anxious dreams
- persistent unwanted thoughts

indications are based on homeopathic materia medica, not clinical tests.

Warnings

Stop use and ask a doctor if symptoms persist or worsen

PREGNANCY OR BREAST FEEDING

If pregnant or breast-feeding ask a health professional before use

Keep out of reach of children

Directions

- spray in mouth at bedtime
- for maximum effect spray in mouth one hour before bed and again at bedtime
- can also be used after waking up in the middle of the night
- use 5 days per week until symptoms are relieved

adults and children 12 years and over | 4-5 sprays per dose
children 2 years to under 12 years | 2-3 sprays per dose
children under 2 years | consult a doctor

Other Information

- do not use if plastic seal around cap is broken or missing.
- store in a cool, dry place.

Inactive Ingredients

Dandelion*, German Chamomile*, Licorice*, Lotus*, Natural Flavor, Purified Water, Sandalwood*, Valerian*, Ylang Ylang*

*flower essence

Questions or Comments?
Call 800.570.0021
Between 9am-5pm PST
info@siddhaflowers.com
siddhaflowers.com

MFD by Siddha Flower Essences
Oxnard, CA 93030

Made in USA

Side Panel

homeopathy and flower essences:

- Jump start your body's natural ability to heal
- Natural, safe and non-habit forming
- No contraindications. May be effectively used with drugs and other supplements
- Alcohol, sugar, dairy and gluten free
- Prepared in purified water with natural preservatives
- Blends time-tested natural medicine with modern technology
- One month supply

FOUNDATIONAL REMEDIES
may be used with targeted remedies

stress relief
daily alignment
emotional detox
deep-seated stress

TARGETED REMEDIES

sleep male virility
healthy hair blood sugar
female balance lung and sinus
muscles and joints throat and voice
youthful skin teeth and gums
happy heart hearing
digestion sight

Principal Display Panel

100% natural - no alcohol
siddha cell salts + flower essences
sleep
Difficulty Falling Asleep
Restless and Sleepless
Agitated Sleep
sugar, dairy and gluten free
Homeopathic Remedy
1 US fl oz (29.6mL)